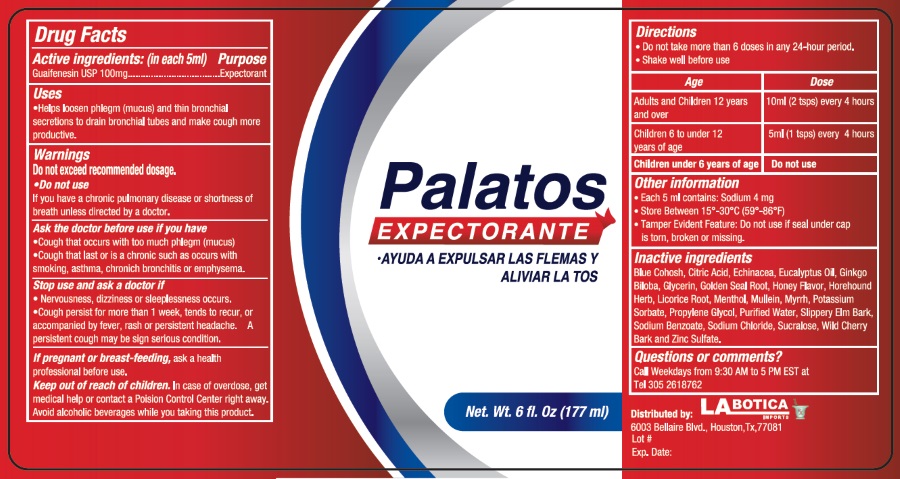 DRUG LABEL: Palatos Expectorante
NDC: 53149-2000 | Form: LIQUID
Manufacturer: All Pharma, LLC
Category: otc | Type: HUMAN OTC DRUG LABEL
Date: 20211231

ACTIVE INGREDIENTS: GUAIFENESIN 100 mg/5 mL
INACTIVE INGREDIENTS: CAULOPHYLLUM THALICTROIDES ROOT; ANHYDROUS CITRIC ACID; ECHINACEA, UNSPECIFIED; EUCALYPTUS CAMALDULENSIS LEAF OIL; GINKGO BILOBA WHOLE; GOLDENSEAL; HOREHOUND; LICORICE; MENTHOL, UNSPECIFIED FORM; VERBASCUM DENSIFLORUM LEAF; MYRRH; POTASSIUM SORBATE; ULMUS RUBRA BARK; SODIUM BENZOATE; PROPYLENE GLYCOL; WATER; SODIUM CHLORIDE; SUCRALOSE; PRUNUS SEROTINA BARK; ZINC SULFATE, UNSPECIFIED FORM; GLYCERIN

ACTIVE INGREDIENT

Acvtive ingredients: (in each 5ml) Purpose

Guaifenesin 100 mg ................................... Expectorant

Purpose

Expectorant

Uses

- Help loosen phlegm (mucus) and thin bronchial secretions to drain bronchial tubes and make cough more productive.

Warnings

Do not exceed recommended dosage

Do not use

- if you have a chronic pulmonary disease or shortness of breath unless directed by a doctor

Ask the doctor before use if you have

- cough that occurs with too much phlegm (mucus)
- cough that lasts or is chronic such as occurs with smoking, asthma, chronic bronchitis or emphysema

Stop use and ask the doctor if

- Nervoisness, dizziness or sleeplessness occurs.
- Cough persists for more than 1 week, tends to recur, or accompanied by fever, rash or persistent headache. A persistent cough may be sign of a serious condition

PREGNANCY OR BREAST FEEDING

If pregnant or breast-feeding, ask a health professional before use.

Keep out of reach of children. In case of overdose, get medical help or contact a Poison Control Center right away.

Directions

- Do not take more than 6 doses in any 24-hour period
- Shake well before use

Age Dose

Adults and children 12 years and over 10 mL (2 tsps) every 4 hours

Children 6 to under 12 years of age. 5 mL (1 tsps) every 4 hours

Children under 6 years of age Do not use

Inactive ingredients

Blue cohosh, citric acid, echinacea, eucalyptus oil, ginkgo biloba, glycerin, gold seal root, honey flavor, horehound herb, licorice root, menthol, mullein, myrrh, potassium sorbate, slippery elm bark, sodium benzoate, propylene glycol, water, sodium chloride, sucralose, wild cherry bark and zinc sulfate.